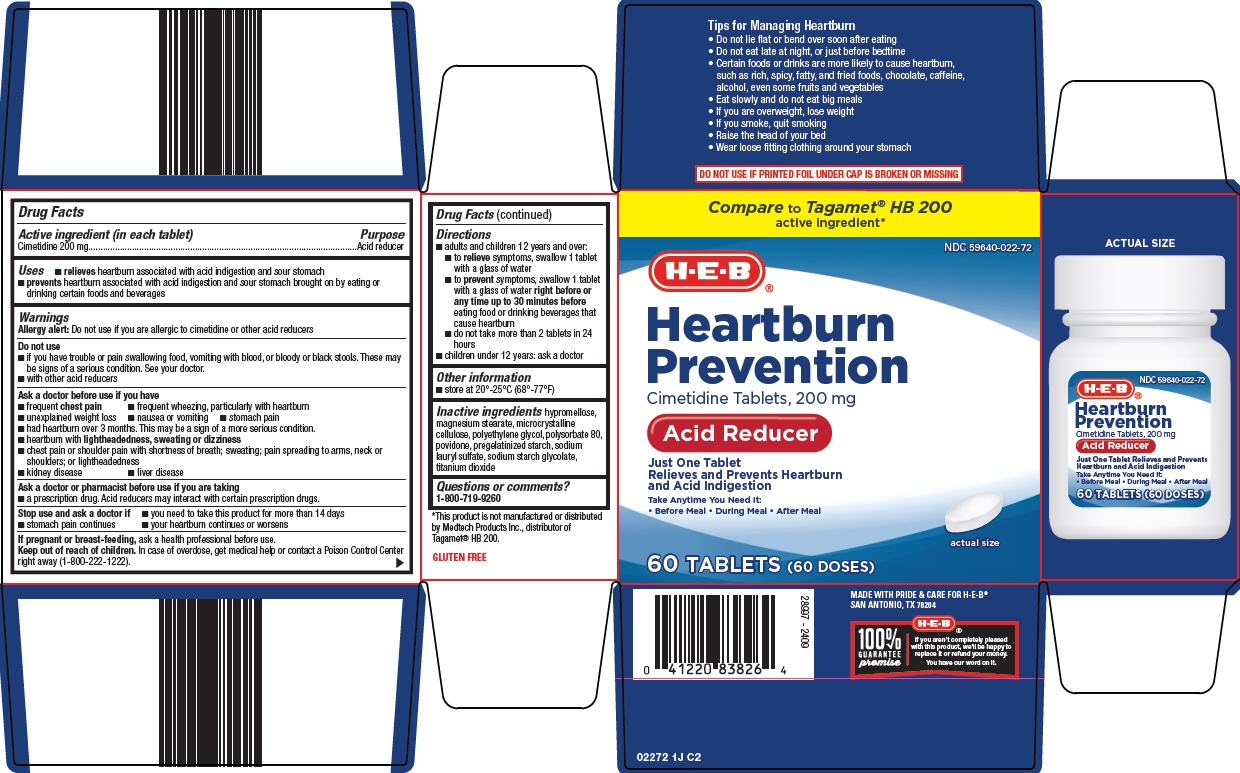 DRUG LABEL: heartburn prevention
NDC: 59640-022 | Form: TABLET, FILM COATED
Manufacturer: H E B
Category: otc | Type: HUMAN OTC DRUG LABEL
Date: 20250826

ACTIVE INGREDIENTS: CIMETIDINE 200 mg/1 1
INACTIVE INGREDIENTS: HYPROMELLOSE, UNSPECIFIED; MAGNESIUM STEARATE; MICROCRYSTALLINE CELLULOSE; POLYETHYLENE GLYCOL, UNSPECIFIED; POLYSORBATE 80; POVIDONE, UNSPECIFIED; SODIUM LAURYL SULFATE; TITANIUM DIOXIDE

HEB Heartburn Prevention Drug Facts

Active ingredient (in each tablet)

Cimetidine 200 mg

Purpose

Acid reducer

Uses

- relieves heartburn associated with acid indigestion and sour stomach
- prevents heartburn associated with acid indigestion and sour stomach brought on by eating or drinking certain foods and beverages

Warnings

Allergy alert: Do not use if you are allergic to cimetidine or other acid reducers

Do not use

- if you have trouble or pain swallowing food, vomiting with blood, or bloody or black stools. These may be signs of a serious condition. See your doctor.
- with other acid reducers

Ask a doctor before use if you have

- frequent chest pain
- frequent wheezing, particularly with heartburn
- unexplained weight loss
- nausea or vomiting
- stomach pain
- had heartburn over 3 months. This may be a sign of a more serious condition.
- heartburn with lightheadedness, sweating or dizziness
- chest pain or shoulder pain with shortness of breath; sweating; pain spreading to arms, neck or shoulders; or lightheadedness
- kidney disease
- liver disease

Ask a doctor or pharmacist before use if you are taking

- a prescription drug. Acid reducers may interact with certain prescription drugs.

Stop use and ask a doctor if

- you need to take this product for more than 14 days
- stomach pain continues
- your heartburn continues or worsens

If pregnant or breast-feeding,

ask a health professional before use.

Keep out of reach of children.

In case of overdose, get medical help or contact a Poison Control Center right away (1-800-222-1222).

Directions

- adults and children 12 years and over:
- to relieve symptoms, swallow 1 tablet with a glass of water
- to prevent symptoms, swallow 1 tablet with a glass of water right before or any time up to 30 minutes before eating food or drinking beverages that cause heartburn
- do not take more than 2 tablets in 24 hours
- children under 12 years: ask a doctor

Other information

- store at 20°-25°C (68°-77°F)

Inactive ingredients

hypromellose, magnesium stearate, microcrystalline cellulose, polyethylene glycol, polysorbate 80, povidone, pregelatinized starch, sodium lauryl sulfate, sodium starch glycolate, titanium dioxide

Questions or comments?

1-800-719-9260

Principal Display Panel

Compare to Tagamet® HB 200 active ingredient

H-E-B®

Heartburn Prevention

Cimetidine Tablets, 200 mg

Acid Reducer

Just One Tablet Relieves and Prevents Heartburn and Acid Indigestion

Take Anytime You Need It:

• Before Meal

• During Meal

• After Meal

actual size

60 TABLETS (60 DOSES)